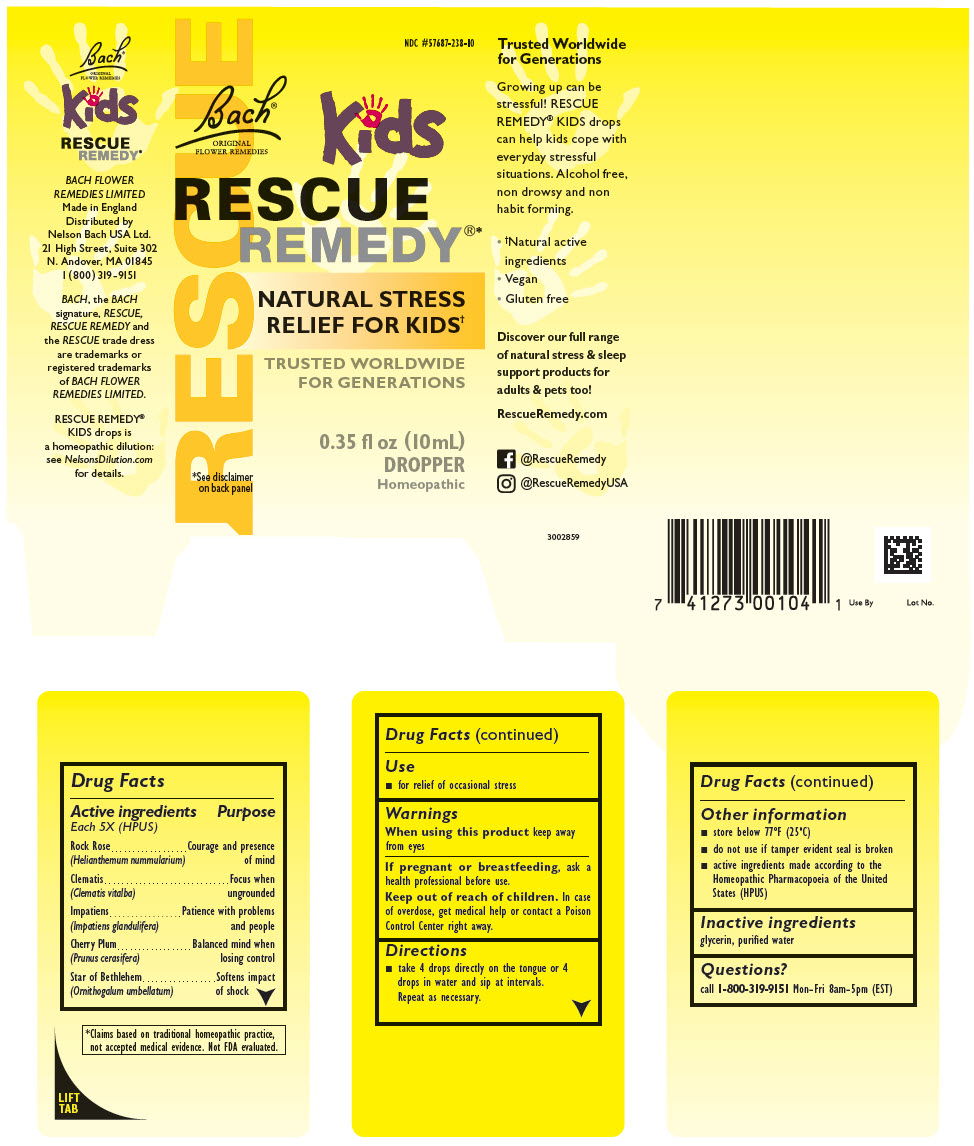 DRUG LABEL: Rescue Remedy Kids
NDC: 57687-238 | Form: SOLUTION
Manufacturer: Nelson Bach USA, Ltd.
Category: homeopathic | Type: HUMAN OTC DRUG LABEL
Date: 20201019

ACTIVE INGREDIENTS: HELIANTHEMUM NUMMULARIUM FLOWER 5 [hp_X]/0.095 mL; CLEMATIS VITALBA FLOWER 5 [hp_X]/0.095 mL; IMPATIENS GLANDULIFERA FLOWER 5 [hp_X]/0.095 mL; PRUNUS CERASIFERA FLOWER 5 [hp_X]/0.095 mL; ORNITHOGALUM UMBELLATUM WHOLE 5 [hp_X]/0.095 mL
INACTIVE INGREDIENTS: Glycerin

Kids
RESCUE®
REMEDY

Drug Facts

ACTIVE INGREDIENT

Active ingredients Each 5X (HPUS) | Purpose
Rock Rose (Helianthemum nummularium) | Courage and presence of mind
Clematis (Clematis vitalba) | Focus when ungrounded
Impatiens (Impatiens glandulifera) | Patience with problems and people
Cherry Plum (Prunus cerasifera) | Balanced mind when losing control
Star of Bethlehem (Ornithogalum umbellatum) | Softens impact of shock

Use

- for relief of occasional stress

Warnings

When using this product keep away from eyes

PREGNANCY OR BREAST FEEDING

If pregnant or breastfeeding, ask a health professional before use.

Keep out of reach of children. In case of overdose, get medical help or contact a Poison Control Center right away.

Directions

- take 4 drops directly on the tongue or 4 drops in water and sip at intervals. Repeat as necessary.

Other information

- store below 77ºF (25ºC)
- do not use if tamper evident seal is broken
- active ingredients made according to the Homeopathic Pharmacopoeia of the United States (HPUS)

Inactive ingredients

glycerin, purified water

Questions?

call 1-800-319-9151 Mon-Fri 8am-5pm (EST)

Distributed by
Nelson Bach USA Ltd.
21 High Street, Suite 302
N. Andover, MA 01845

PRINCIPAL DISPLAY PANEL - 10 mL Bottle Carton

RESCUE

NDC #57687-238-10

Bach®
ORIGINAL
FLOWER REMEDIES

kids
RESCUE
REMEDY®*

NATURAL STRESS
RELIEF FOR KIDS†

TRUSTED WORLDWIDE
FOR GENERATIONS

0.35 fl oz (10mL)
DROPPER
Homeopathic

*See disclaimer
on back panel